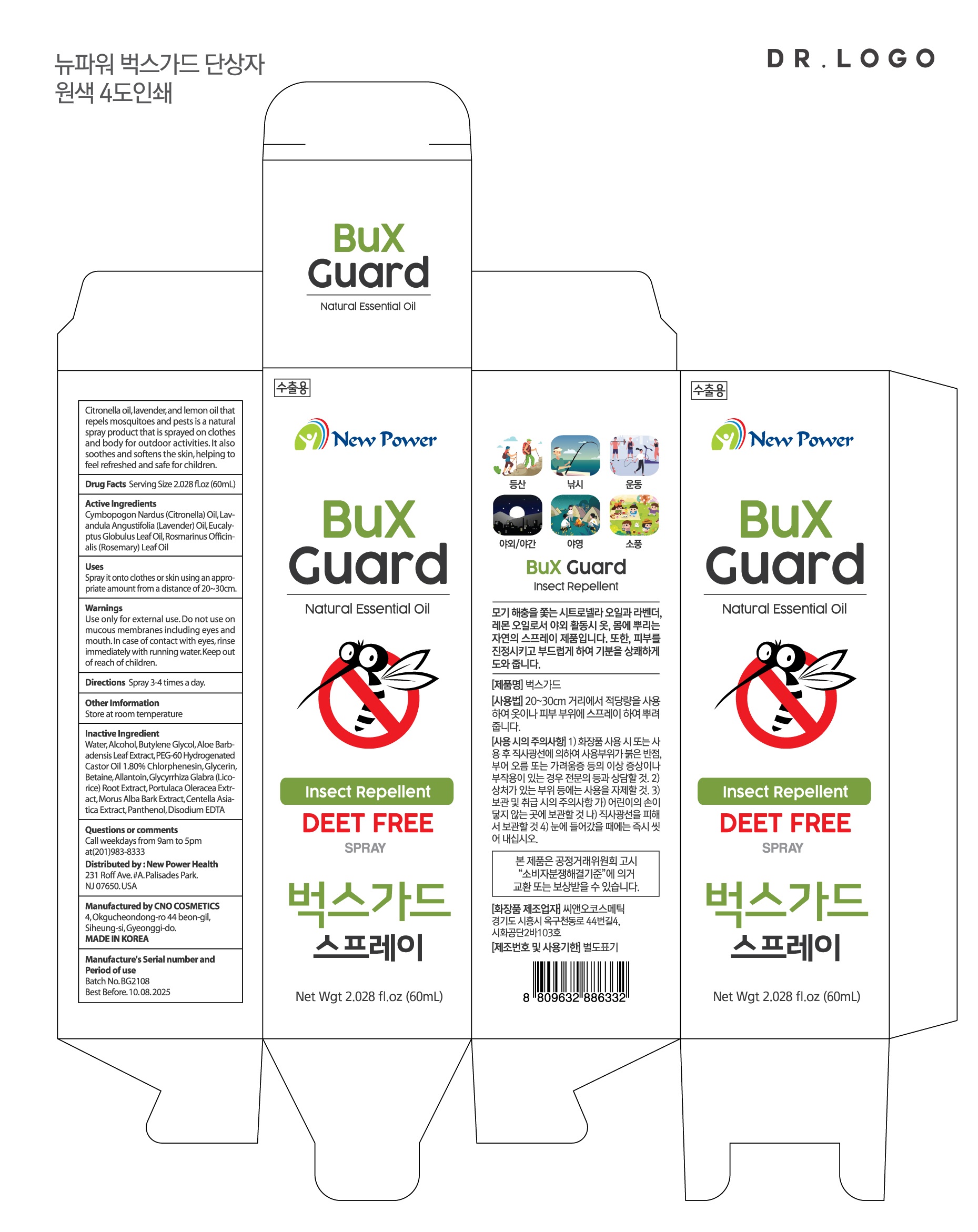 DRUG LABEL: BUX GUARD
NDC: 82145-0004 | Form: LIQUID
Manufacturer: Aloe Vera Korea Co.,Ltd.
Category: otc | Type: HUMAN OTC DRUG LABEL
Date: 20210729

ACTIVE INGREDIENTS: LAVENDER OIL 10 g/100 mL
INACTIVE INGREDIENTS: WATER; BUTYLENE GLYCOL

Drug Facts

ACTIVE INGREDIENT

lavender oil, citronella oil,

INACTIVE INGREDIENT

water, alcohol, butylene glycol etc

PURPOSE

mosquito repellents that prevent access to mosquitoes.

keep out of reach of the children

INDICATIONS AND USAGE

You can spray it on your skin or clothes.

do not use for the following people: infants under six months

do not use excessive amounts or for long periods of time beyond the required

do not use it in an enclosed area

DOSAGE AND ADMINISTRATION

for external use only